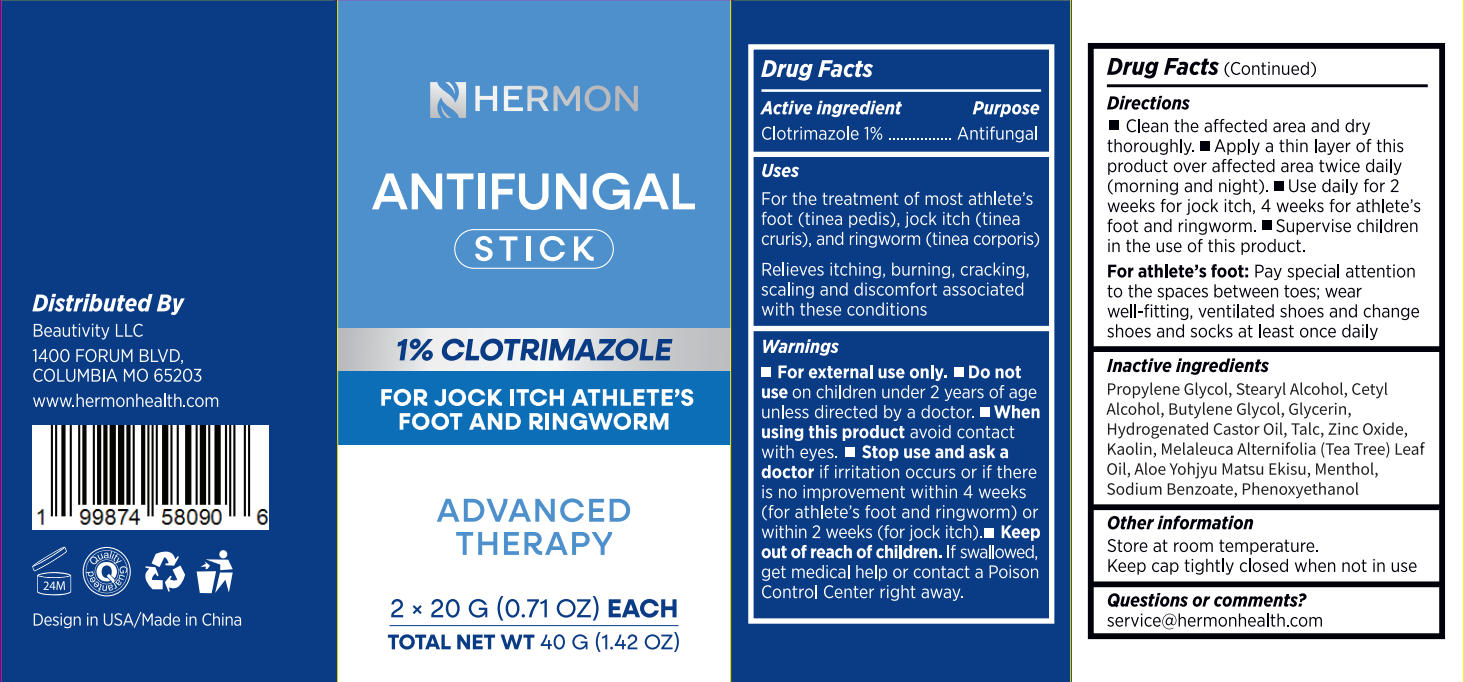 DRUG LABEL: Hermon Antifungal Stick
NDC: 85398-021 | Form: STICK
Manufacturer: Beautivity LLC
Category: otc | Type: HUMAN OTC DRUG LABEL
Date: 20251231

ACTIVE INGREDIENTS: CLOTRIMAZOLE 0.4 g/40 g
INACTIVE INGREDIENTS: BUTYLENE GLYCOL; ALOE; PHENOXYETHANOL; STEARYL ALCOHOL; KAOLIN; SODIUM BENZOATE; CETYL ALCOHOL; PROPYLENE GLYCOL; GLYCERIN; HYDROGENATED CASTOR OIL; ZINC OXIDE; TALC; MENTHOL, (+)-; MELALEUCA ALTERNIFOLIA (TEA TREE) LEAF OIL

Initial Drug Listing - Hermon Antifungal Stick

ACTIVE INGREDIENT

Clotrimazole 1%

PURPOSE

Antifungal

DOSAGE AND ADMINISTRATION

- For the treatment of most athlete's foot (tinea pedis), jock itch (tineacruris), and ringworm (tinea corporis)
- Relieves itching, burning, cracking,scaling and discomfort associated with these conditions

WARNINGS

For external use only.

DO NOT USE

on children under 2 years of age unless directed by a doctor.

WHEN USING

avoid contact with eyes.

STOP USE

if irritation occurs or if there is no improvement within 4 weeks(for athlete's foot and ringworm) or within 2 weeks (for jock itch).

KEEP OUT OF REACH OF CHILDREN

lf swallowed,get medical help or contact a Poison Control Center right away.

INDICATIONS AND USAGE

- Clean the affected area and dry thoroughly.
- Apply a thin layer of this product over affected area twice daily(morning and night).
- Use daily for 2weeks for jock itch, 4 weeks for athlete'sfoot and ringworm.
- Supervise childrenin the use of this product.

For athlete's foot:

Pay special attentionto the spaces between toes; wearwell-fitting, ventilated shoes and change shoes and socks at least once daily

INACTIVE INGREDIENT

Propylene Glycol, Stearyl Alcohol, Cetyl Alcohol, Butylene Glycol, Glycerin,Hydrogenated Castor Oil, Talc, Zinc Oxide,Kaolin, Melaleuca Alternifolia (Tea Tree) Leaf Oil, Aloe Yohjyu Matsu Ekisu, Menthol,Sodium Benzoate, Phenoxyethanol

OTHER SAFETY INFORMATION

Store at room temperature.Keep cap tightly closed when not in use

QUESTIONS

service@hermonhealth.com